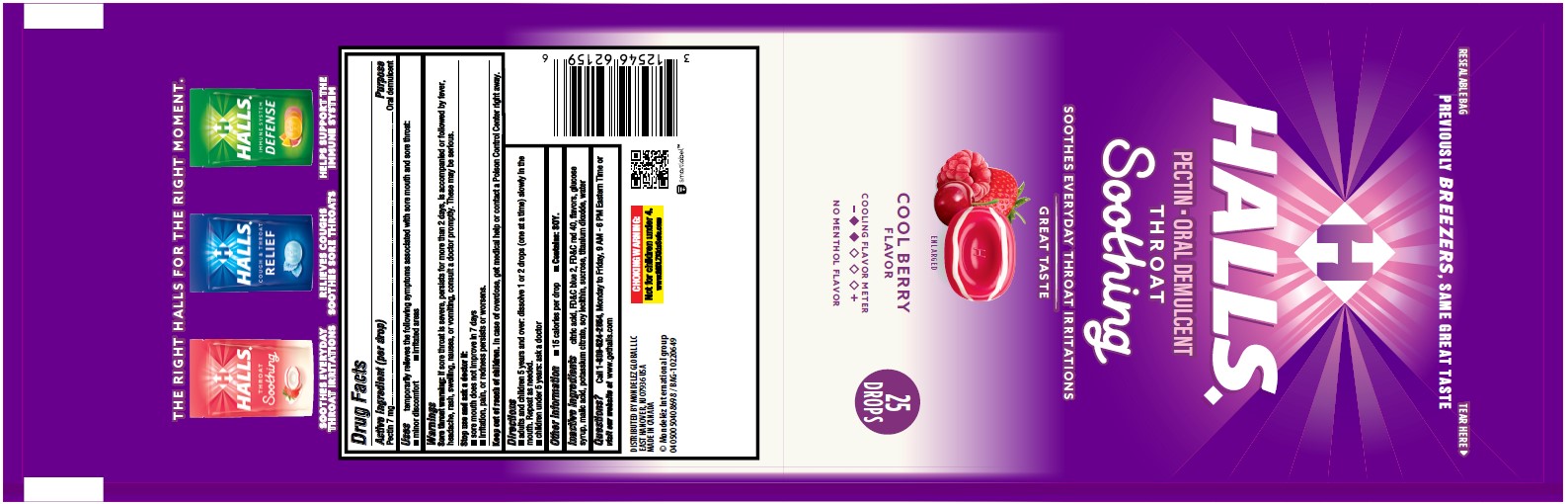 DRUG LABEL: Breezers
NDC: 12546-151 | Form: LOZENGE
Manufacturer: Mondelez Global LLC
Category: otc | Type: HUMAN OTC DRUG LABEL
Date: 20241220

ACTIVE INGREDIENTS: PECTIN 7 mg/1 1
INACTIVE INGREDIENTS: ANHYDROUS CITRIC ACID; FD&C BLUE NO. 2; FD&C RED NO. 40; MALIC ACID; POTASSIUM CITRATE; LECITHIN, SOYBEAN; SUCROSE; TITANIUM DIOXIDE; WATER; CORN SYRUP

Halls cool berry bag

Active Ingredient

<(per drop) Pectin 7 mg>

Purpose

<Oral demulcent>

Uses

<temporarily relieves the following symptoms associated with sore mouth and sore throat:

- minor discomfort
- irritated areas>

Warnings

<Sore throat warning: if sore throat is severe, persists for more than 2 days, is accompanied or followed by fever, headache, rash, swelling, nausea, or vomiting, consult a doctor promptly. These may be serious.>

Stop use and ask a doctor if

- sore mouth does not improve in 7 days
- irritation, pain, or redness persists or worsens

Keep out of reach of children

In case of overdose, get medical help or contact a Poison Control Center right away

Directions

- adults and children 5 years and over: dissolve 1 or 2 drops (one at a time) slowly in the mouth. Repeat as needed.
- children under 5 years, ask a doctor

Other information

<

- 15 calories per drop
- Contains: SOY.>

Inactive ingredients

<citric acid, FDC blue 2, FDC red 40, flavors, glucose syrup, malic acid, potassium citrate, soy lecithin, sucrose, titanium dioxide, water>

Questions

<Call 1-800-524-2854, Monday to Friday, 9 AM - 6 PM Eastern Time or visit our website at www.gethalls.com>